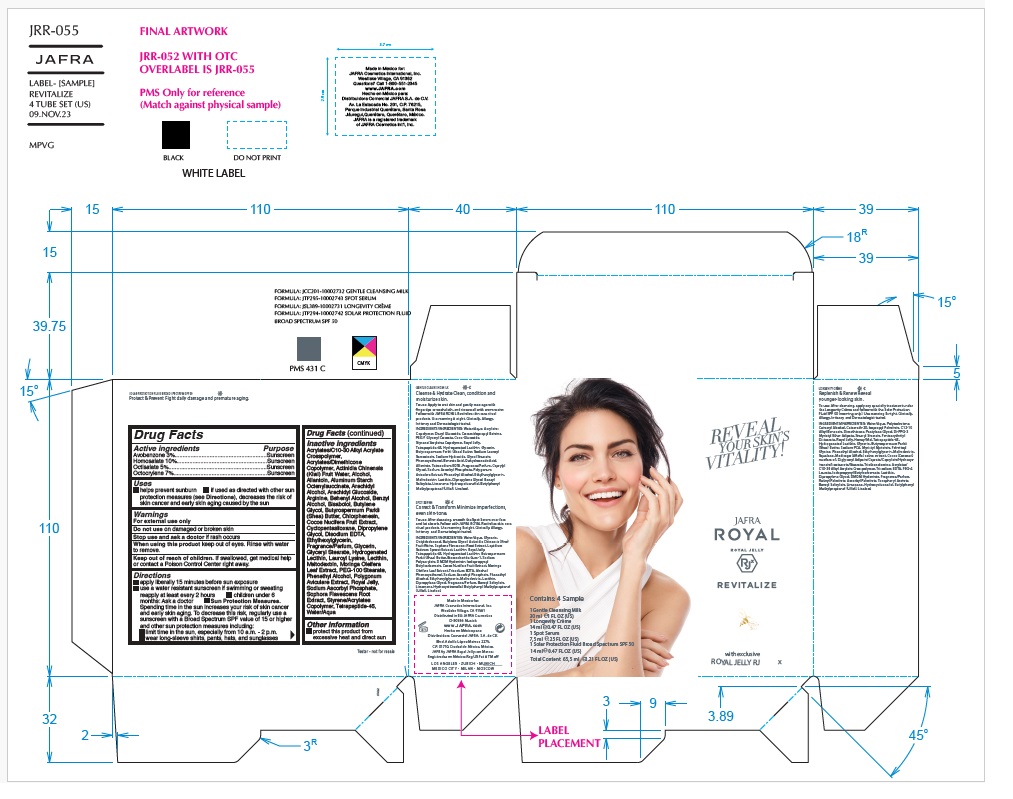 DRUG LABEL: JAFRA ROYAL REVITALIZE 4 TUBE SET
NDC: 68828-522 | Form: KIT | Route: TOPICAL
Manufacturer: Distribuidora Comercial Jafra, S.A. de C.V.
Category: otc | Type: HUMAN OTC DRUG LABEL
Date: 20250109

ACTIVE INGREDIENTS: AVOBENZONE 3 g/100 mL; HOMOSALATE 10 g/100 mL; OCTISALATE 5 g/100 mL; OCTOCRYLENE 10 g/100 mL
INACTIVE INGREDIENTS: CARBOMER COPOLYMER TYPE B (ALLYL PENTAERYTHRITOL CROSSLINKED); KIWI FRUIT OIL; ALCOHOL; ALLANTOIN; ALUMINUM STARCH OCTENYLSUCCINATE; ARACHIDYL ALCOHOL; ARACHIDYL GLUCOSIDE; ARGININE; DOCOSANOL; BENZYL ALCOHOL; LEVOMENOL; BUTYLENE GLYCOL; SHEA BUTTER; CHLORPHENESIN; COCONUT; CYCLOMETHICONE 5; DIPROPYLENE GLYCOL; EDETATE DISODIUM; ETHYLHEXYLGLYCERIN; GLYCERIN; HYDROGENATED SOYBEAN LECITHIN; LAUROYL LYSINE; LECITHIN, SOYBEAN; MALTODEXTRIN; MORINGA OLEIFERA LEAF; PEG-100 MONOSTEARATE; PHENYLETHYL ALCOHOL; POLYGONUM AVICULARE TOP; ROYAL JELLY; SODIUM ASCORBYL PHOSPHATE; SOPHORA FLAVESCENS ROOT; STYRENE/ACRYLAMIDE COPOLYMER (500000 MW); WATER; GLYCERYL MONOSTEARATE

JAFRA ROYAL REVITALIZE 4 TUBE SET

Active Ingredients

Avobenzone 3%

Homosalate 10%

Octisalate 5%

Octocrylene 7%

Purpose

Sunscreen

Uses

- helps prevent sunburn
- if used as directed with other sun protection measures (see Directions), decreases the risk of skin cancer and early skin aging caused by the sun.

Warnings

For external use only

Do not use on damaged or broken skin

When using this productkeep out of eyes. Rinse with water to remove.

Stop use and ask a doctor if rash occurs

Keep out of reach of children.If swallowed, get medical help or contact a Poison Control Center right away.

Directions

- apply liberally 15 minutes before sun exposure
- use a water resistant sunscreen if swimming or sweating
- reapply at least every 2 hours.
- children under 6 months of age: Ask a doctor
- Sun Protection Measures.Spending time in the sun increases your risk of skin cancer and early skin aging. To decrease this risk, regularly use a sunscreen with a Broad-Spectrum SPF value of 15 or higher and other sun protection measures including:

• limit your time in the sun, especially from 10 a.m. – 2 p.m.

• wear long-sleeved shirts, pants, hats, and sunglasses

Inactive ingredients

Acrylates/C10-30 Alkyl Acrylate Crosspolymer, Acrylates/Dimethicone Copolymer, Actinidia Chinensis (Kiwi) Fruit Water, Alcohol, Allantoin,

Aluminum Starch Octenylsuccinate, Arachidyl Alcohol, Arachidyl Glucoside, Arginine, Behenyl Alcohol, Benzyl Alcohol, Bisabolol, Butylene Glycol,

Butyrospermum Parkii (Shea) Butter, Chlorphenesin, Cocos Nucifera Fruit Extract, Cyclopentasiloxane, Dipropylene Glycol, Disodium EDTA,

Ethylhexylglycerin, Fragrance/Parfum, Glycerin, Glyceryl Stearate, Hydrogenated Lecithin, Lauroyl Lysine, Lecithin, Maltodextrin, Moringa Oleifera

Leaf Extract, PEG-100 Stearate, Phenethyl Alcohol, Polygonum Aviculare Extract, Royal Jelly,

Sodium Ascorbyl Phosphate, Sophora Flavescens Root Extract, Styrene/Acrylates Copolymer, Tetrapeptide-45, Water/Aqua

Other information

- protect this product from excessive heat and direct sun